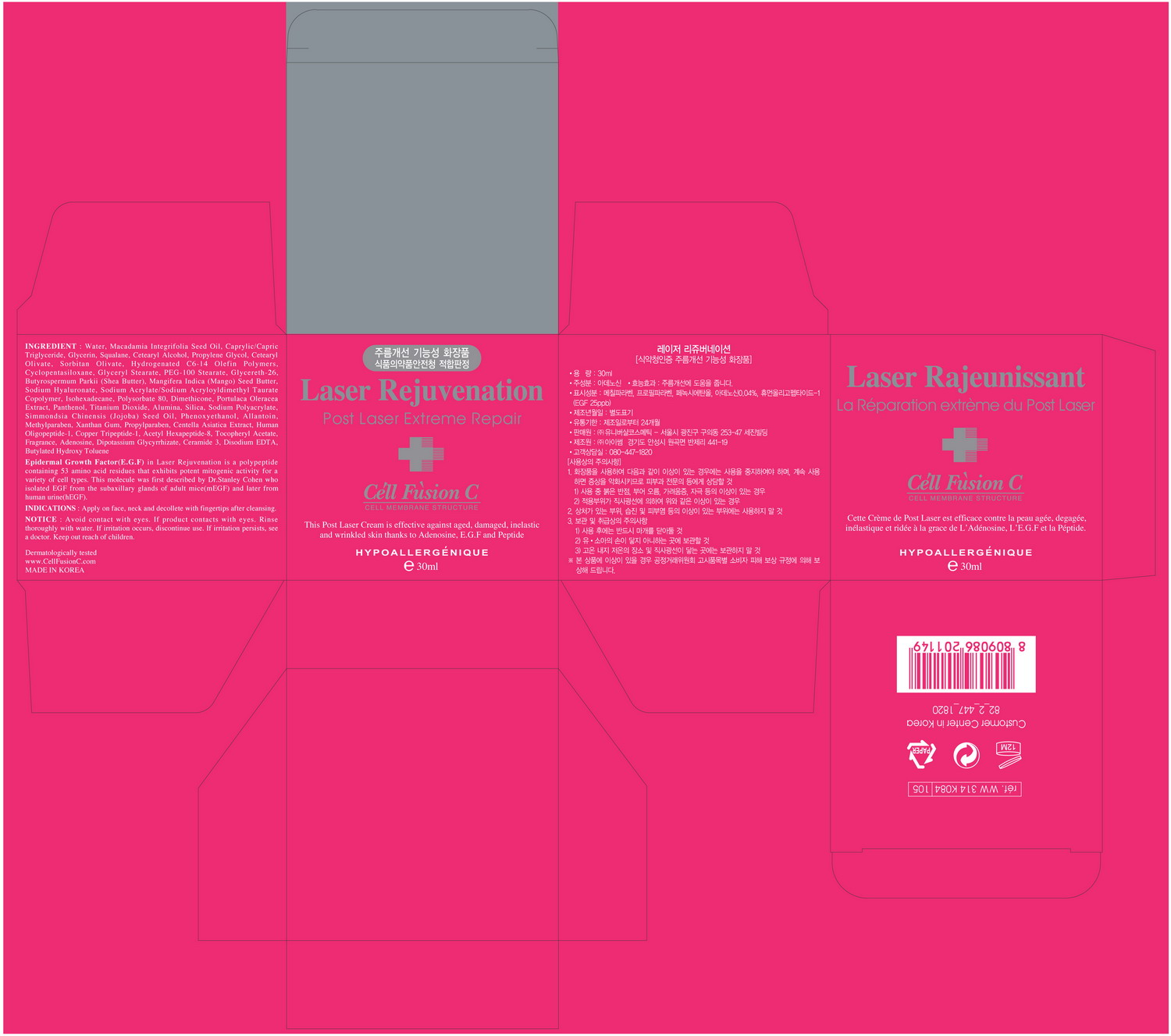 DRUG LABEL: Laser Rejuvenation
NDC: 52554-5001 | Form: CREAM
Manufacturer: Universal Cosmetic Co., Ltd
Category: otc | Type: HUMAN OTC DRUG LABEL
Date: 20100819

ACTIVE INGREDIENTS: ADENOSINE 0.00004 mL/1 mL; ACETYL HEXAPEPTIDE-3 0.0001 mL/1 mL; CENTELLA ASIATICA 0.001 mL/1 mL

Drug Facts

ACTIVE INGREDIENT

Active Ingredients: Adenosine, Copper Tripeptide, Acetyl Hexapeptide, Centella Asiatica Extract

Uses
■ Helps to restore damaged skin after high or low power laser treatment including fraxel and IPL etc and medical treatment such as MTS and peeling.
■ Helps to repair aging skin including wrinkles and decrease in elasticity etc.

Warning
For external use only
When using this product
■ Avoid contact with eyes. If contacts with eyes, rinse thoroughly with water.
■ If irritation occurs, discontinue use. If irritation persists, see a doctor.
Keep out of reach of the children

INDICATIONS AND USAGE

Direction
■ Apply after cleansing.
■ Apply appropriate amounts onto the skin defect and damaged areas and then absorb patting gently, morning and night.

Warning
For external use only
When using this product
■ Avoid contact with eyes. If contacts with eyes, rinse thoroughly with water.
■ If irritation occurs, discontinue use. If irritation persists, see a doctor.
Keep out of reach of the children